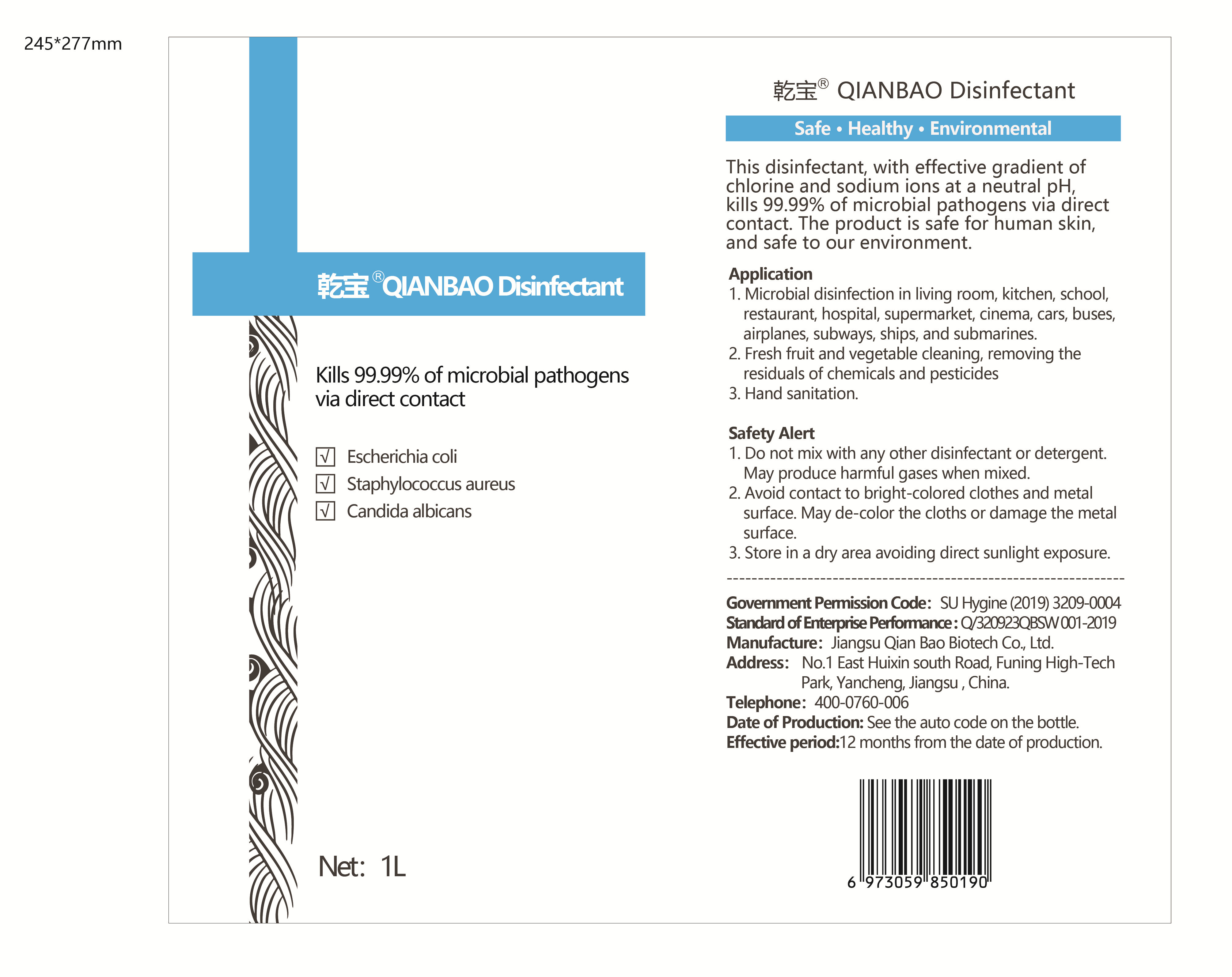 DRUG LABEL: QIAN BAO Disinfectant
NDC: 56012-001 | Form: LIQUID
Manufacturer: Jiangsu Qian Bao Biotech Co.,Ltd.
Category: otc | Type: HUMAN OTC DRUG LABEL
Date: 20200416

ACTIVE INGREDIENTS: SODIUM HYPOCHLORITE 1 mg/1 L
INACTIVE INGREDIENTS: WATER; SODIUM CHLORIDE

INACTIVE INGREDIENT

Deionized water Sodium chloride

DOSAGE AND ADMINISTRATION

Store in a dry area avoiding direct sunlight exposure.

WARNINGS

1. Do not mix with any other disinfectant or detergent.May produce harmful gases when mixed.
2. Avoid contact to bright-colored clothes and metal surface. May de-color the cloths or damage the metal surface.

INDICATIONS AND USAGE

1. Microbial disinfection in living room, kitchen, school,restaurant, hospital, supermarket, cinema, cars, buses,airplanes, subways, ships, and submarines.
2. Fresh fruit and vegetable cleaning, removing the residuals of chemicals and pesticides
3. Hand sanitation.

PURPOSE

Disinfection
Sterilization
No Rinseing

keep out of reach of children

ACTIVE INGREDIENT

Sodium Hypochlorite 0.1%